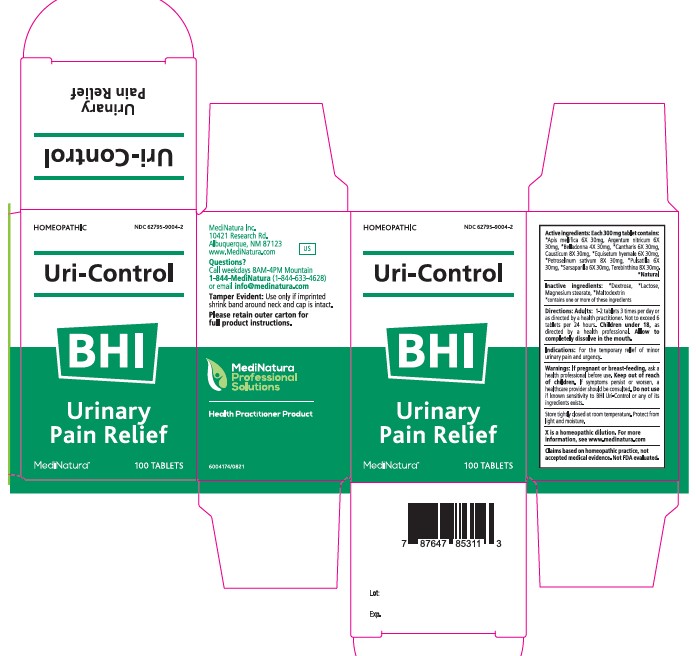 DRUG LABEL: BHI Uri-Control
NDC: 62795-9004 | Form: TABLET
Manufacturer: MediNatura Inc
Category: homeopathic | Type: HUMAN OTC DRUG LABEL
Date: 20230413

ACTIVE INGREDIENTS: APIS MELLIFERA 6 [hp_X]/1 1; SILVER NITRATE 6 [hp_X]/1 1; ATROPA BELLADONNA 4 [hp_X]/1 1; LYTTA VESICATORIA 6 [hp_X]/1 1; CAUSTICUM 8 [hp_X]/1 1; EQUISETUM HYEMALE 6 [hp_X]/1 1; PETROSELINUM CRISPUM 8 [hp_X]/1 1; PULSATILLA VULGARIS 6 [hp_X]/1 1; SMILAX ORNATA ROOT 6 [hp_X]/1 1; TURPENTINE OIL 8 [hp_X]/1 1
INACTIVE INGREDIENTS: LACTOSE; MAGNESIUM STEARATE; MALTODEXTRIN; DEXTROSE

BHI Uri-Control

Keep out of reach of children

Indications:

For the temporary relief of minor
urinary pain and urgency.

Warnings:

If pregnant or breast-feeding, ask a
health professional before use. Keep out of reach
of children. If symptoms persist or worsen, a
healthcare provider should be consulted. Do not use
if known sensitivity to BHI Uri-Control or any of its
ingredients exists.

Directions:

Adults: 1-2 tablets 3 times per day or
as directed by a health practitioner. Not to exceed 6
tablets per 24 hours. Children under 18, as
directed by a health professional. Allow to
completely dissolve in the mouth

Active ingredients:

Each 300 mg tablet contains:
*Apis mellifica 6X 30mg, Argentum nitricum 6X
30mg, *Belladonna 4X 30mg, *Cantharis 6X 30mg,
Causticum 8X 30mg, *Equisetum hyemale 6X 30mg,
*Petroselinum sativum 8X 30mg, *Pulsatilla 6X
30mg, *Sarsaparilla 6X 30mg, Terebinthina 8X 30mg.
*Natural

Inactive ingredients:

*Dextrose, *Lactose,
Magnesium stearate, *Maltodextrin
*contains one or more of these ingredients

Purpose

Urinary Pain Relief